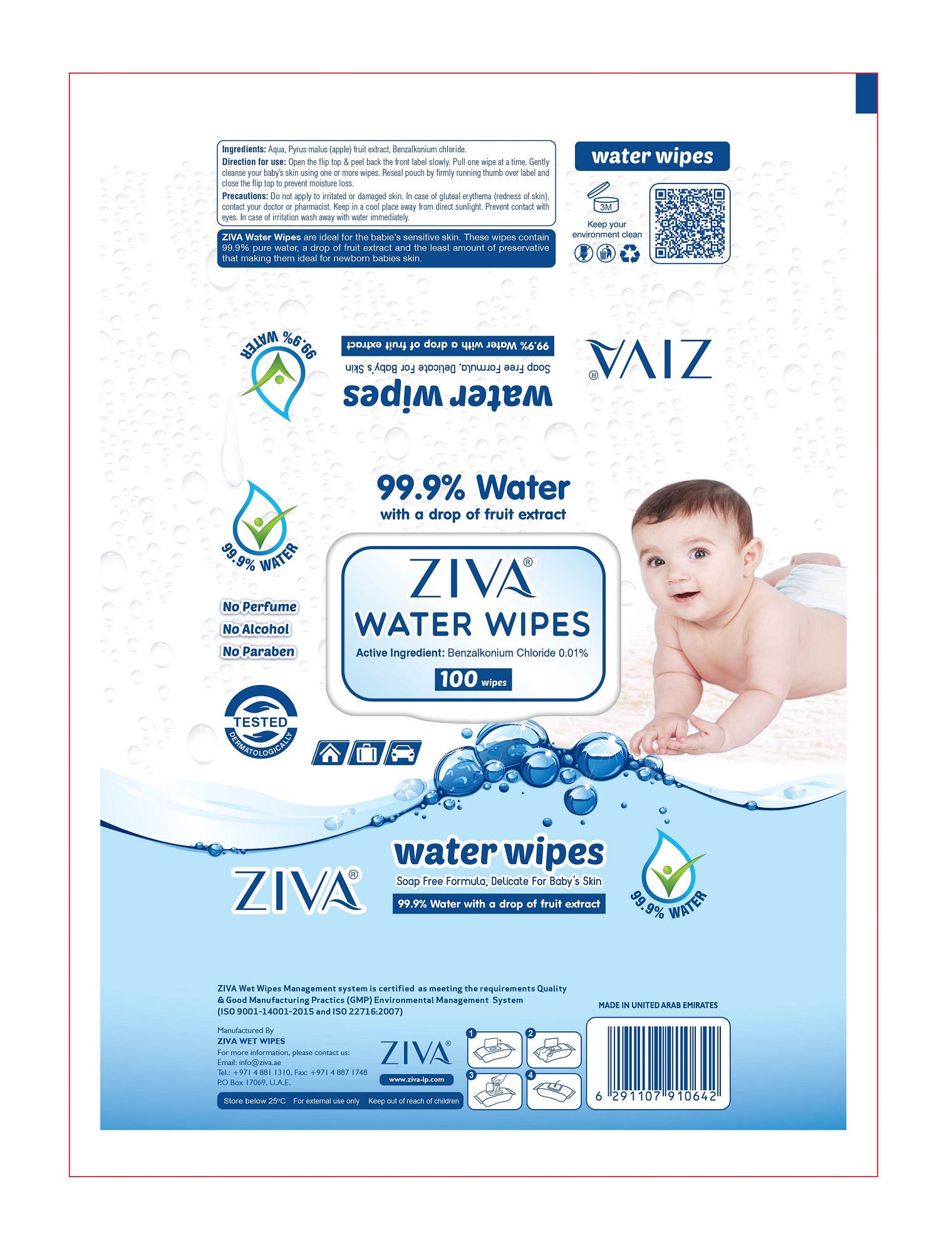 DRUG LABEL: ZIVA WATER WIPES
NDC: 81450-006 | Form: CLOTH
Manufacturer: Ziva Wetwipes FZCo
Category: otc | Type: HUMAN OTC DRUG LABEL
Date: 20211223

ACTIVE INGREDIENTS: BENZALKONIUM CHLORIDE 0.01 g/100 mL
INACTIVE INGREDIENTS: APPLE FRUIT OIL; WATER

Drug Facts

Active Ingredient:

Benzalkonium Chloride 0.01%

Direction for use

For external use only. Open the flip top & peel back the front label slowly. Pull one wipe at a time. Gently cleanse your baby's skin using one or more wipes. Reseal pouch by firmly running thumb over label and close the flip top to prevent moisture loss.

Precautions:

Do not apply to irritated or damaged skin. In case of gluteal erythema (redness of skin), contact your doctor or pharmacist. Keep in a cool place away from direct sunlight. Prevent contact with eyes. In case of irritation wash away with water immediately.

Other information

Store below 25°C

Ingredients

Aqua, Pyrus Malus (apple) fruit extract, Benzalkonium Chloride.